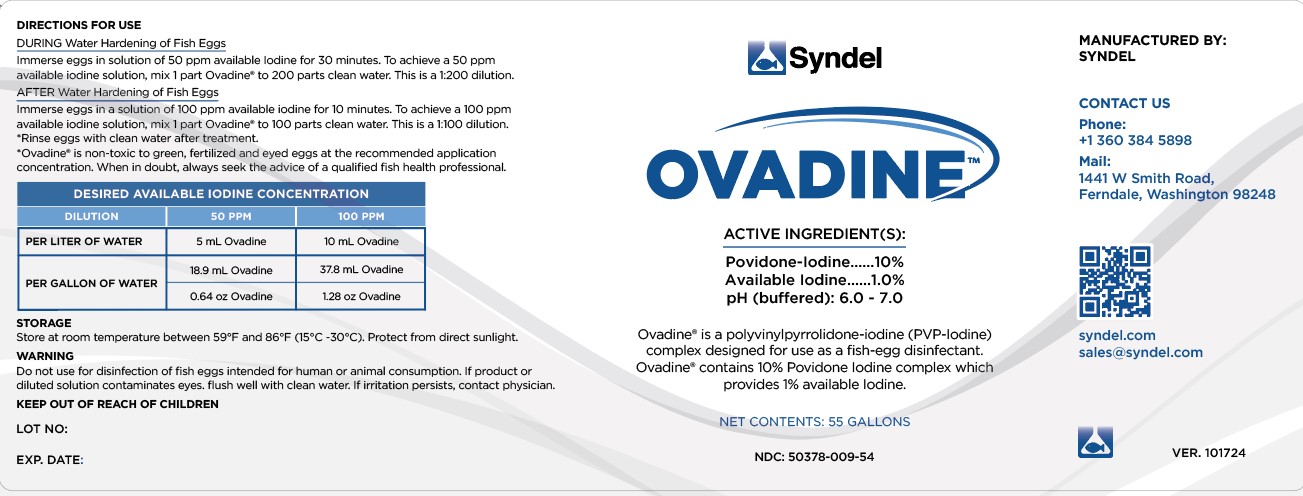 DRUG LABEL: Ovadine
								
NDC: 50378-009 | Form: SOLUTION
Manufacturer: Western Chemical Inc.
Category: animal | Type: OTC ANIMAL DRUG LABEL
Date: 20250120

ACTIVE INGREDIENTS: Povidone-Iodine 100 g/1 L
INACTIVE INGREDIENTS: Water 900 g/1 L

Fish Egg Disinfectant Ovadine® (Buffered PVP Iodine) Ovadine® is a polyvinylpyrrolidone iodine(PVP-Iodine)complex designed for use as a fish-egg disinfectant. Ovadine contains 10% Povidone Iodine complex which provides 1% available iodine.

DESCRIPTION

DURING Water hardening of fish eggs
· Immerse eggs in a solution of 50 PPM available Iodine for 30 minutes. To achieve a 50 PPM available
iodine solution, mix 1 part Ovadine® to 200 parts clean water. This is a 1:200 dilution.
AFTER Water hardening of fish eggs
· Immerse eggs in a solution of 100 PPM available Iodine for 10 minutes. To achieve a 100 PPM
available iodine solution, mix 1 part Ovadine® to 100 parts clean water. This is a 1:100 dilution.
Rinse eggs with clean water after treatment.

Ovadine® is non-toxic to green, fertilized and eyed eggs at the recommended application concentration. When in
doubt, always seek the advice of a qualified fish health professional.

AMOUNT OF OVADINE PER UNIT OF WATER

Desired Available Iodine Concentration

50 ppm 100 ppm
(1:200 dilution) (1:100 dilution)
Per Liter
of Water 5 ml Ovadine 10 ml Ovadine

Per Gallon 18.9 ml Ovadine 37.8 ml Ovadine
of Water 0.64 oz Ovadine 1.28 oz Ovadine

Storage

Store at room temperature between 59°F and 86°F (15°C and 30°C). Protect from direct sunlight.

Warning

Do not use for disinfection of fish eggs intended for human or animal consumption. If product or
diluted solution contaminates eyes, flush well with clean water. If irritation persists, contact a physician.

Keep out of reach of children